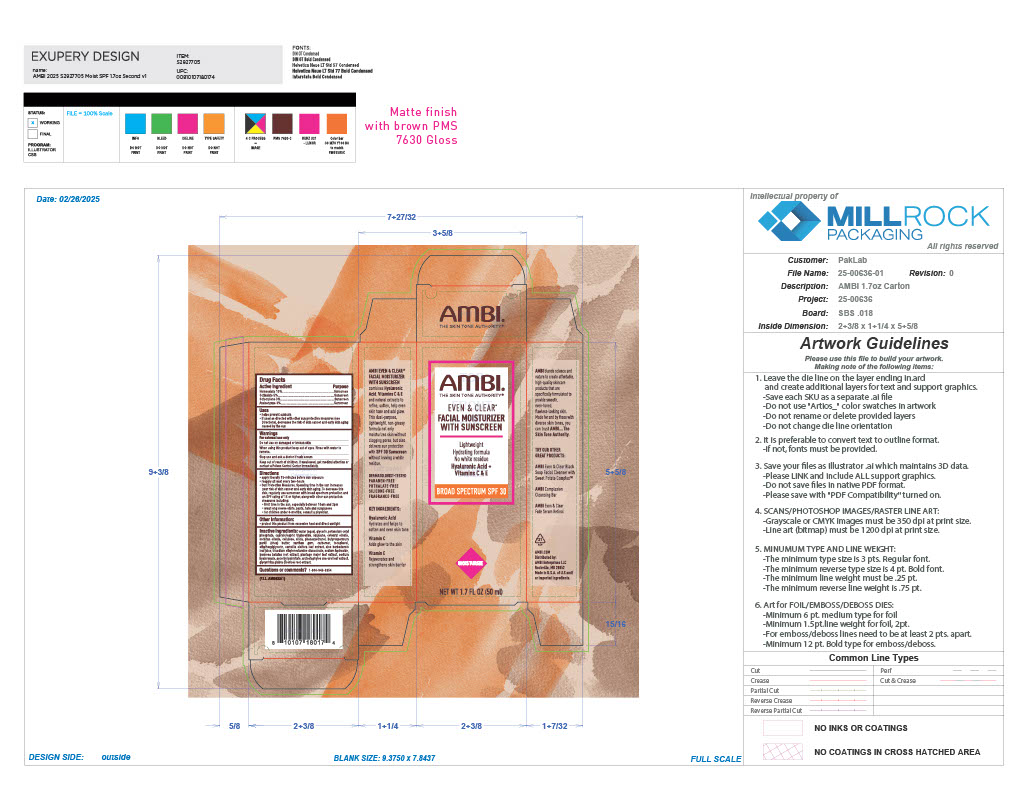 DRUG LABEL: Ambi Even and Clear Facial Moisturizer
NDC: 73453-112 | Form: CREAM
Manufacturer: 73453-112
Category: otc | Type: HUMAN OTC DRUG LABEL
Date: 20251222

ACTIVE INGREDIENTS: OCTISALATE 5 mg/1 mL; AVOBENZONE 3 mg/1 mL; HOMOSALATE 15 mg/1 mL; OCTOCRYLENE 3 mg/1 mL
INACTIVE INGREDIENTS: PLANTAGO MAJOR LEAF; CETEARYL OLIVATE; ASCORBYL PALMITATE; ETHYLHEXYLGLYCERIN; CAMELLIA OLEIFERA LEAF; CARBOMER; ARCTOSTAPHYLOS UVA-URSI LEAF; TRISODIUM ETHYLENEDIAMINE DISUCCINATE; SODIUM HYDROXIDE; GLYCYRRHIZA GLABRA (LICORICE) ROOT; POTASSIUM CETYL PHOSPHATE; CAPRYLIC/CAPRIC TRIGLYCERIDE; SQUALANE; XANTHAN GUM; GLYCERIN; PHENOXYETHANOL; SODIUM HYALURONATE; TOCOPHEROL; ALOE BARBADENSIS LEAF JUICE; SORBITAN OLIVATE; BUTYROSPERMUM PARKII (SHEA) BUTTER; WATER; CELLULOSE, OXIDIZED; IPOMOEA BATATAS LEAF

Ambi Even and Clear Facial Moisturizer with Sunscreen

Active ingredient

Homosalate 15%

Octisalate 5%

Octocrylene 3%

Avobenzone 3%

Purpose

Sunscreen

Uses

helps prevent sunburn. if used s directed with other sun protection measures (see Directions), decrease the risk of skin cancer and early skin aging caused by the sun.

Warnings

For external use only

do not use on damaged or broken skin

When using this product keep out of eyes. Rinse with water to remove.

Stop use and ask a doctor if rash occurs

Keep out of reach of children

If swallowed, get medical attention or contact a Poison Control Center immediately

Directions

apply liberally 15-minutes before sun exposure. reapply at least every two hours. Sun Protection Measures. Spending time in the sun increases your risk of skin cancer and early skin aging. To decrease this risk, regularly use sunscreen with broad spectrum protection and an SPF rating of 15 or higher, along with other sun proetection measures inlcuding: limit time in the sun, especially betwen 10am and 2pm. wear long sleeve shirts, pants, hats and sunglasses. for children under 6-months, consult a physician.

Other information:

protect this product from excessive heat and direct sunlight

Inactive ingredients:

water (aqua), glycerin, potassium cetyl phosphate, caprylic/capric triglyceride, squalane, cetearyl olivate, sorbitan olivate, cellulose, silica, phenoxyethanol, butyrospermum parkii (shea) butter, xanthan gum, carbomer, tocopherol, ethylhexylglycerin, camellia oleifera leaf extract, alo barbadensis leaf juice, trisodium ethylenediamine disuccinate, sodium hydroxide, ipomoea batatas root extract, plantago major leaf extract, sodium hyaluronate, ascorbyl palmitate, arctostaphylos uva-ursi leaf extract, glycyrrhiza glabra (licorice) root extract.

Questions or comments?

1-800-946-6354